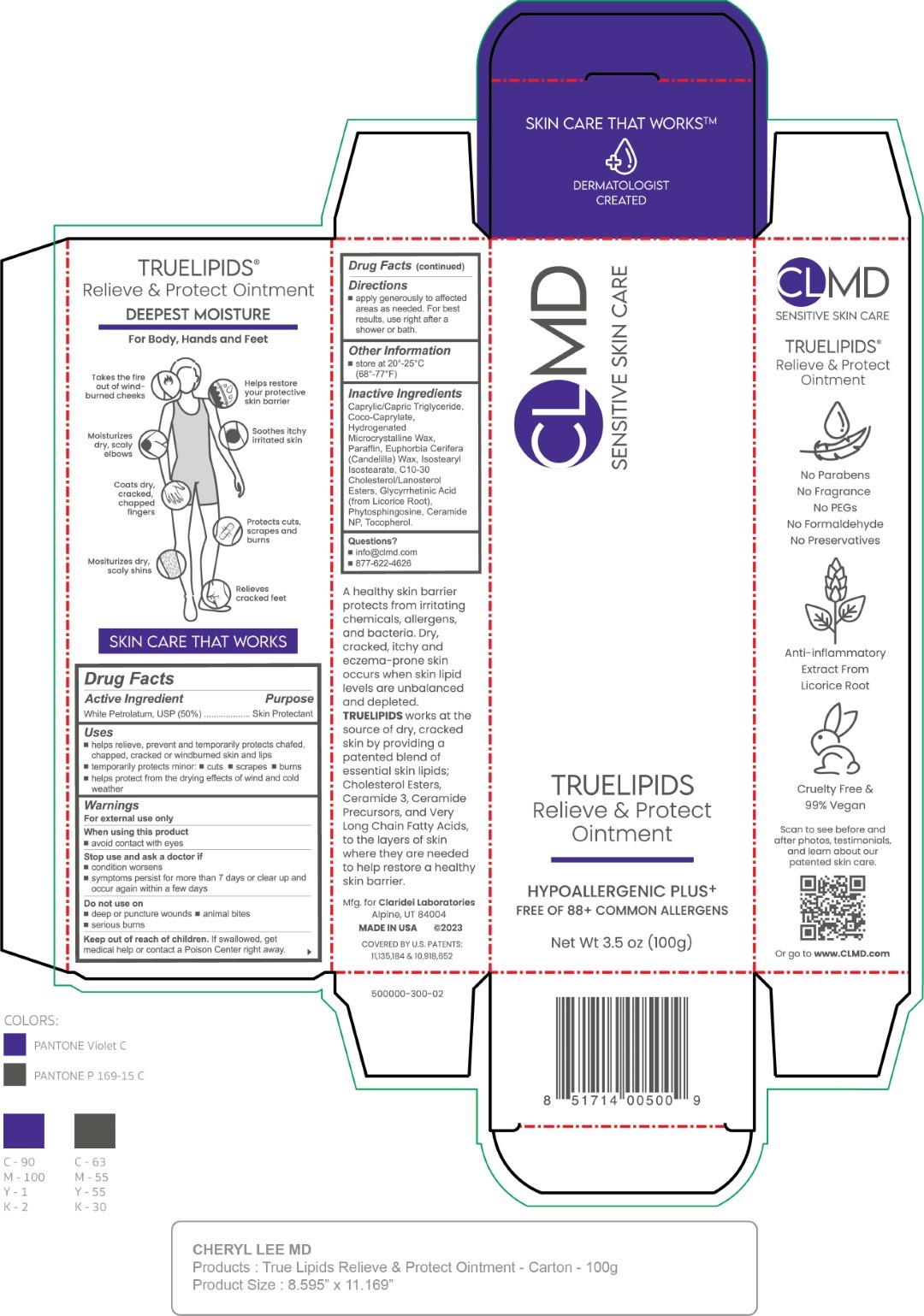 DRUG LABEL: TrueLipids Relieve and Protect
NDC: 61387-254 | Form: OINTMENT
Manufacturer: Claridei Laboratories, Inc.
Category: otc | Type: HUMAN OTC DRUG LABEL
Date: 20251215

ACTIVE INGREDIENTS: PETROLATUM 50 g/100 g
INACTIVE INGREDIENTS: MEDIUM-CHAIN TRIGLYCERIDES; CERAMIDE 3; COCO-CAPRYLATE; CANDELILLA WAX; ENOXOLONE; C10-30 CHOLESTEROL/LANOSTEROL ESTERS; ISOSTEARYL ISOSTEARATE; MICROCRYSTALLINE WAX; PARAFFIN; PHYTOSPHINGOSINE

CL MD TrueLipids Relieve and Protect Ointment

Active Ingredient Purpose

White Petrolatum, USP (50%) Skin Protectant

Uses

- helps relieve, prevent and temporarily protects chafed, chapped, cracked or windburned skin and lips
- temporarily protects minor:
- cuts
- scrapes
- burns
- helps protect from the drying effects of wind and cold weather

Keep out of reach of children. If swallowed, get medical help or contact a Poison Control Center right away.

Uses

Stop use and ask a doctor if:

- condition worsens
- symptoms persist for more than 7 days or clear up and occur again within a few days

Warnings

For external use only

When using this product

- avoid contact with eyes

Do not use on:

- deep or puncture wounds
- animal bites
- serious burns

Directions

- apply generously to affected areas as needed. For best results, use right after a shower or bath

Inactive Ingredients

Caprylic/Capric Triglyceride, Coco-Caprylate, Hydrogenated Microcrystalline Wax, Paraffin, Euphorbia Cerifera (Candelilla) Wax, Isostearyl Isostearate, C10-C30 Cholesterol/Lanosterol Esters, Glycyrrhetinic Acid (from Licorice Root), Phytosphingosine, Ceramide NP, Tocopherol.

PACKAGE LABEL

CLMD

Sensitive Skin Care

Truelipids

Relieve & Protect Ointment

Net Wt 3.5 oz (100g)